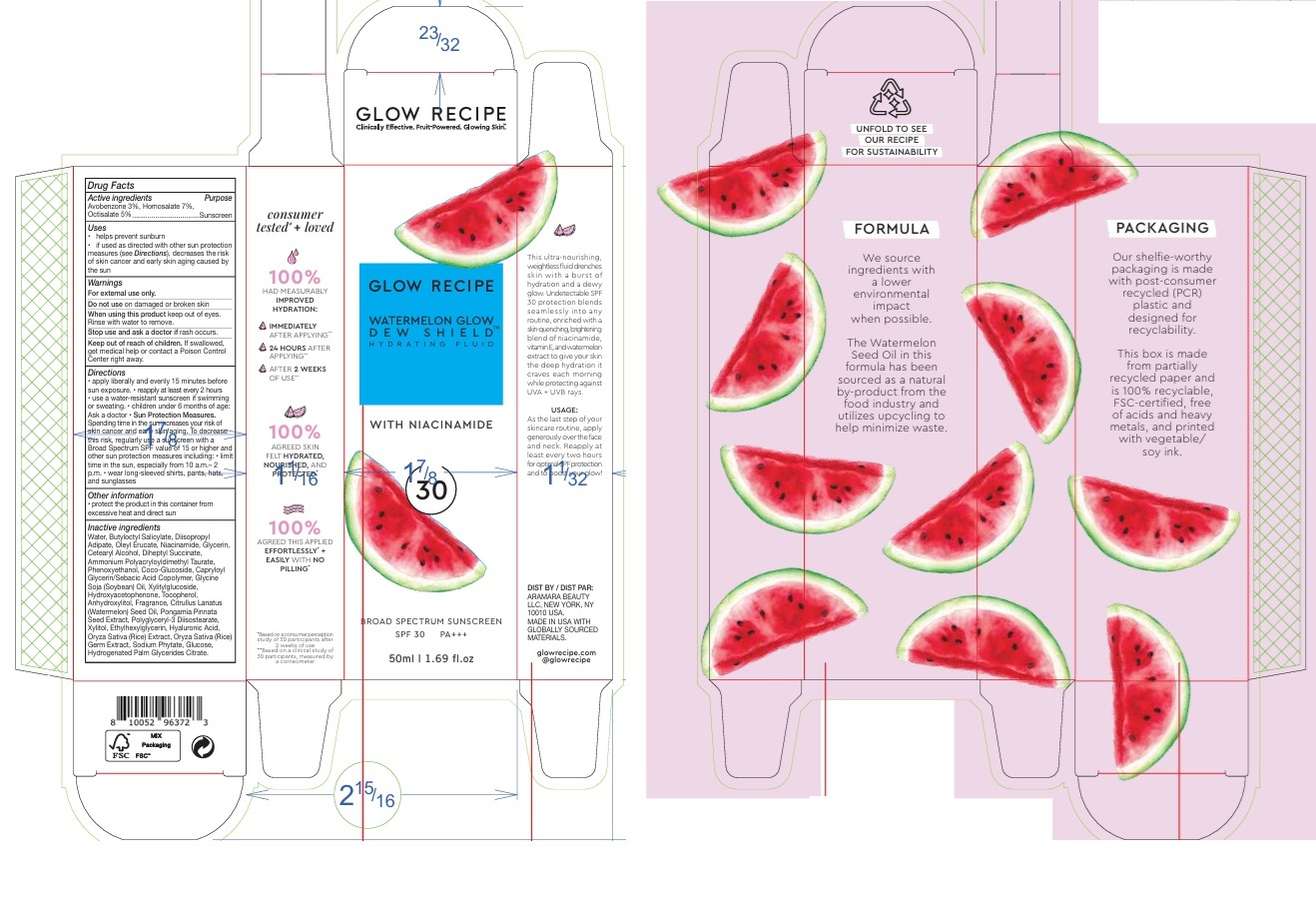 DRUG LABEL: GLOW RECIPE WATERMELON GLOW DEW SHIELD HYDRATING FLUID SPF 30
NDC: 72156-004 | Form: LOTION
Manufacturer: Aramara Beauty LLC dba Glow Recipe
Category: otc | Type: HUMAN OTC DRUG LABEL
Date: 20250127

ACTIVE INGREDIENTS: OCTISALATE 50 mg/1 mL; HOMOSALATE 70 mg/1 mL; AVOBENZONE 30 mg/1 mL
INACTIVE INGREDIENTS: ANHYDROXYLITOL; HYDROGENATED PALM GLYCERIDES CITRATE; GLUCOSE; WATER; SODIUM PHYTATE; HYDROXYACETOPHENONE; DIISOPROPYL ADIPATE; BUTYLOCTYL SALICYLATE; OLEYL ERUCATE; CAPRYLOYL GLYCERIN/SEBACIC ACID COPOLYMER (2000 MPA.S); WATERMELON SEED OIL; GLYCERIN; CETOSTEARYL ALCOHOL; DIHEPTYL SUCCINATE; AMMONIUM POLYACRYLOYLDIMETHYL TAURATE; PHENOXYETHANOL; COCO-GLUCOSIDE; SOYBEAN OIL; NIACINAMIDE; XYLITYLGLUCOSIDE; TOCOPHEROL; PONGAMIA PINNATA SEED; POLYGLYCERYL-3 DIISOSTEARATE; XYLITOL; ETHYLHEXYLGLYCERIN; HYALURONIC ACID; RICE GERM

GLOW RECIPE WATERMELON GLOW DEW SHIELD HYDRATING FLUID SPF 30

Active ingredients

Avobenzone 3%
Homosalate 7%
Octisalate 5%

Purpose

Sunscreen

Uses

- helps prevent sunburn
- if used as directed with other sun protection measures (see Directions), decreases the risk of skin cancer and early skin aging caused by the sun

Warnings

For external use only.

Do not use

on damaged or broken skin

When using this product

keep out of eyes. Rinse with water to remove.

Stop use and ask a doctor if

rash occurs.

Keep out of reach of children.

If swallowed, get medical help or contact a Poison Control Center right away.

Directions

- apply liberally and evenly 15 minutes before sun exposure.
- reapply at least every 2 hours
- use a water-resistant sunscreen if swimming or sweating
- children under 6 months of age: Ask a doctor
- Sun Protection Measures. Spending time in the sun increases your risk of skin cancer and early skin aging. To decrease this risk, regularly use a sunscreen with a Broad Spectrum SPF value of 15 or higher and other sun protection measures including:
- limit time in the sun, especially from 10 a.m. - 2 p.m.
- wear long-sleeved shirts, pants, hats, and sunglasses

Other information

- protect the product in this container from excessive heat and direct sun

Inactive ingredients

Water, Butyloctyl Salicylate, Diisopropyl Adipate, Oleyl Erucate, Niacinamide, Glycerin, Cetearyl Alcohol, Diheptyl Succinate, Ammonium Polyacryloyldimethyl Taurate, Phenoxyethanol, Coco-Glucoside, Capryloyl Glycerin/Sebacic Acid Copolymer, Glycine Soja (Soybean) Oil, Xylitylglucoside, Hydroxyacetophenone, Tocopherol, Anhydroxylitol, Fragrance, Citrullus Lanatus (Watermelon) Seed Oil, Pongamia Pinnata Seed Extract, Polyglyceryl-3 Diisostearate, Xylitol, Ethylhexylglycerin, Hyaluronic Acid, Oryza Sativa (Rice) Extract, Oryza Sativa (Rice) Germ Extract, Sodium Phytate, Glucose, Hydrogenated Palm Glycerides Citrate.